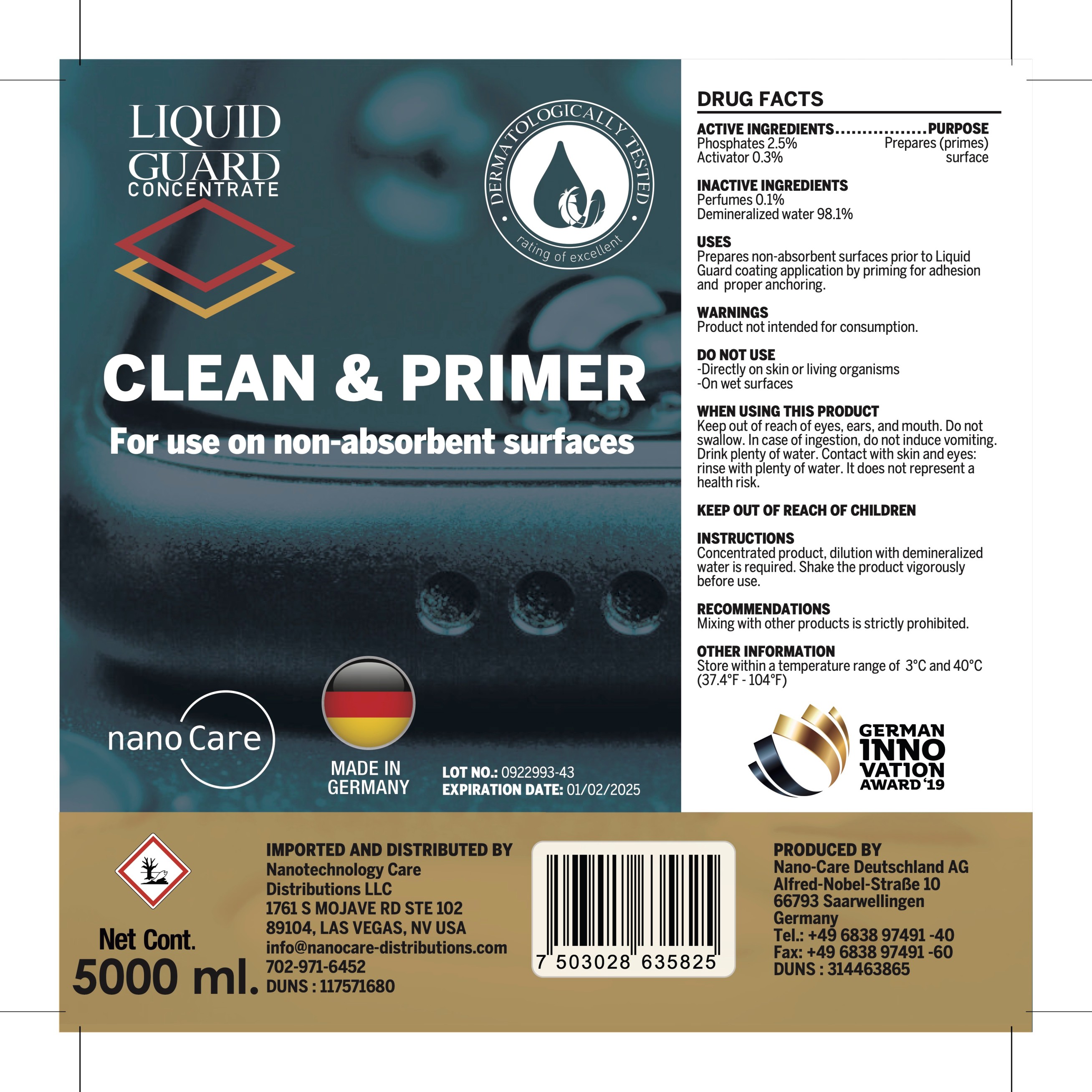 DRUG LABEL: LIQUIDGUARD
NDC: 79836-500 | Form: LIQUID
Manufacturer: Nano Care Deutschland AG
Category: otc | Type: HUMAN OTC DRUG LABEL
Date: 20200809

ACTIVE INGREDIENTS: PHOSPHATE ION 2.5 g/100 mL
INACTIVE INGREDIENTS: WATER 98.1 mL/100 mL

The liquid guard is manufactured using only the following United States Pharmacopoeia (USP) grade ingredients in the preparation of the product (percentage in final product formulation) consistent with World Health Organization (WHO) recommendations:

The firm does not add other active or inactive ingredients. Different or additional ingredients may impact the quality and potency of the product.

Active Ingredient(s)

Phosphates 2.5 % v/v. Purpose: Liquid Guard

PURPOSE

Liquid Guard

INDICATIONS AND USAGE

Liquid Guard to help reduce bacteria that potentially can cause disease.

Warnings

For external use only. Keep out of reach of eyes, ears, and mouth

Do not use

Keep out od reach of childrens

When using this product keep out of eyes, ears, and mouth. In case of contact with eyes, rinse eyes thoroughly with water.
Stop use and ask a doctor if irritation or rash occurs. These may be signs of a serious condition.
Keep out of reach of children. If swallowed, get medical help or contact a Poison Control Center right away.

Stop use and ask a doctor if irritation or rash occurs. These may be signs of a serious condition.

Keep out of reach of children. If swallowed, get medical help or contact a Poison Control Center right away.

DOSAGE AND ADMINISTRATION

Place enough product to clean the infected area. Do not use of wet surfaces / skin.

STORAGE AND HANDLING

Store between 15-30C (59-86F)
Avoid freezing and excessive heat above 40C (104F)

Inactive ingredients

purified water USP

Maximum 1000000000 mL in 1 CONTAINER (79836-500-01)

5000 mL NDC: 79836-500-01